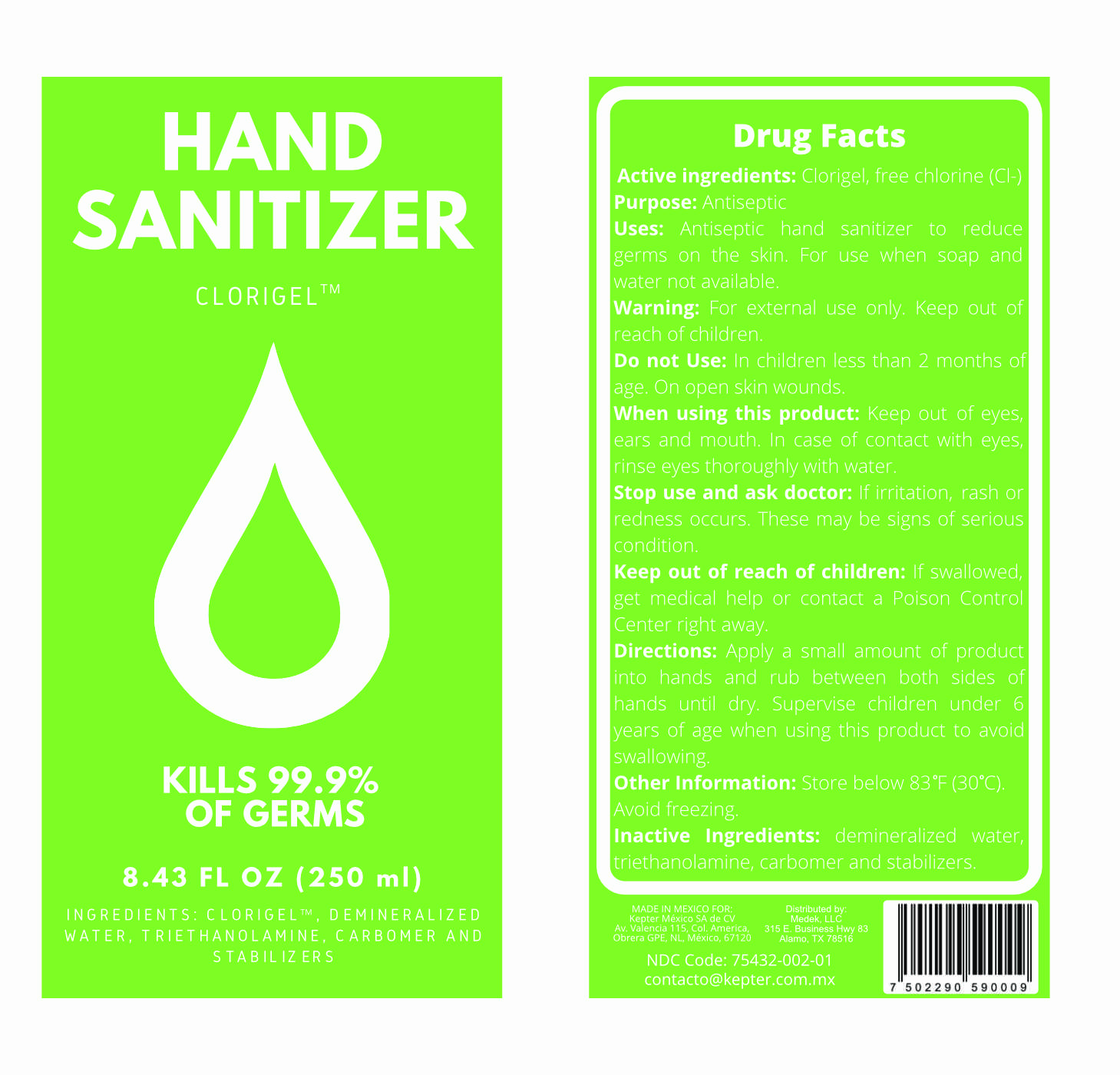 DRUG LABEL: Hand Sanitizer
NDC: 75432-002 | Form: GEL
Manufacturer: Medek, LLC
Category: otc | Type: HUMAN OTC DRUG LABEL
Date: 20200604

ACTIVE INGREDIENTS: HYPOCHLOROUS ACID 0.0005 mg/100 mL
INACTIVE INGREDIENTS: TROLAMINE 1.2 mL/100 mL; EDETIC ACID 0.05 mL/100 mL; WATER; CARBOMER 940 1 mL/100 mL

Hand Sanitizer - Hypochlorous Acid

This is a hand sanitizer manufactured using only the following United States Pharmacopoeia (USP) grade ingredients:

Hypochlorous Acid (0.0005% volume/volume (v/v)).

Triethanolamine (1.2% v/v).

Edetic Acid (0.05% v/v).

Carbopol (1.0% v/v).

Demineralized water.

Active Ingredient(s)

Hypochlorous Acid 0.0005% v/v. Purpose: Antiseptic

Purpose

Antiseptic, Hand Sanitizer

Use

Antiseptic hand sanitizer to reduce germs on skin. For use when soap and water are not available.

Warnings

For external use only. Keep out of reach of children.

Do not use

- in children less than 2 months of age
- on open skin wounds

When using this product keep out of eyes, ears, and mouth. In case of contact with eyes, rinse eyes thoroughly with water.
Stop use and ask a doctor: if irritation, rash or redness occurs. These may be signs of a serious condition.
Keep out of reach of children: If swallowed, get medical help or contact a Poison Control Center right away.

Stop use and ask a doctor: if irritation, rash or redness occurs. These may be signs of a serious condition.

Keep out of reach of children. If swallowed, get medical help or contact a Poison Control Center right away.

Directions

Apply a small amount of product into hands and rub between both sides of hands until dry. Supervise children under 6 years of age when using this product to avoid swallowing.

Other information

Store below 83F (30C)

Avoid freezing.

Inactive ingredients

demineralized water, triethanolamine, carbomer and stabilizers

Package Label - Principal Display Panel

250 mL NDC: 75432-002-01